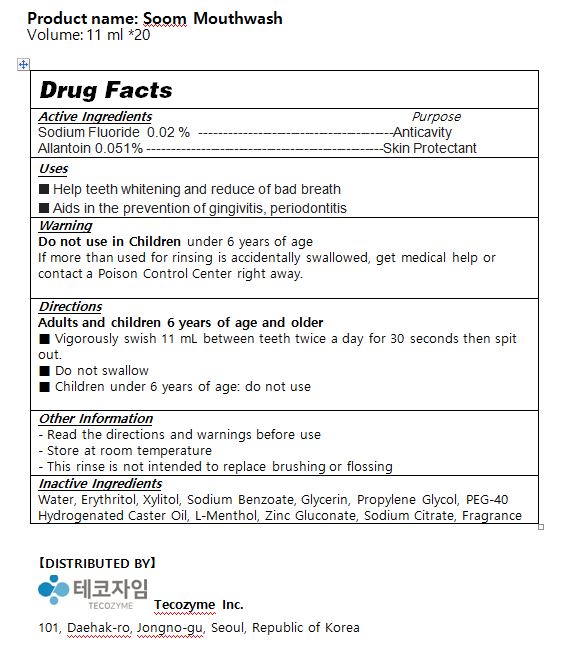 DRUG LABEL: Soom Mouthwash
NDC: 79717-0001 | Form: LIQUID
Manufacturer: TECOZYME INC
Category: otc | Type: HUMAN OTC DRUG LABEL
Date: 20200724

ACTIVE INGREDIENTS: SODIUM FLUORIDE 0.02 g/100 mL
INACTIVE INGREDIENTS: XYLITOL; WATER; ALLANTOIN

ACTIVE INGREDIENT

Sodium Fluoride, allantoin

PURPOSE

■ Help teeth whitening and reduce of bad breath

■ Aids in the prevention of gingivitis, periodontitis

Keep out of reach of children

INDICATIONS AND USAGE

Adults and children 6 years of age and older

■ Vigorously swish 11 mL between teeth twice a day for 30 seconds then spit out.

■ Do not swallow

■ Children under 6 years of age: do not use

Do not use in Children under 6 years of age

If more than used for rinsing is accidentally swallowed, get medical help or contact a Poison Control Center right away.

INACTIVE INGREDIENT

Water, Erythritol, Xylitol, Sodium Benzoate, Glycerin, Propylene Glycol, PEG-40 Hydrogenated Caster Oil, L-Menthol, Zinc Gluconate, Sodium Citrate, Fragrance

DOSAGE AND ADMINISTRATION

For dental use only